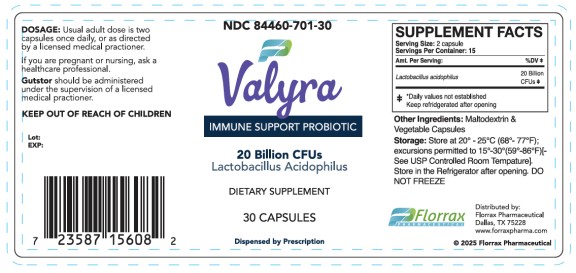 DRUG LABEL: Valyra
NDC: 84460-701 | Form: CAPSULE
Manufacturer: Florrax Pharmaceutical
Category: other | Type: DIETARY SUPPLEMENT
Date: 20260209

ACTIVE INGREDIENTS: LACTOBACILLUS ACIDOPHILUS 2000000000 [CFU]/1 1
INACTIVE INGREDIENTS: MALTODEXTRIN

Valyra

SUPPLEMENT FACTS

Serving Size: 2 capsules

Serving Per Container: 15

Amt. Per Serving: %DV
Lactobacillus Acidophilus 20 Billion CFUs

*Daily values not established
Keep refrigerated after opening

Dosage

Usual adult dose is two capsules once daily, or as directed by a licensed medical practitioner.

Warning

If you are pregnant or nursing, ask a healthcare professional.

Gutstor should be administered under the supervision of a licensed medical practitioner.

KEEP OUT OF REACH OF CHILDREN

HEALTH CLAIM

Store at 20○ - 25○C (68○ - 77○F);

Excursions permitted to 15○ – 30○ (59○ – 86○F);

See USP Controlled Room Temperature].

Store in the Refrigerator after opening.

DO NOT FREEZE

PRINCIPAL DISPLAY PANEL

NDC 84460-701-30
Valyra
30 Capsules